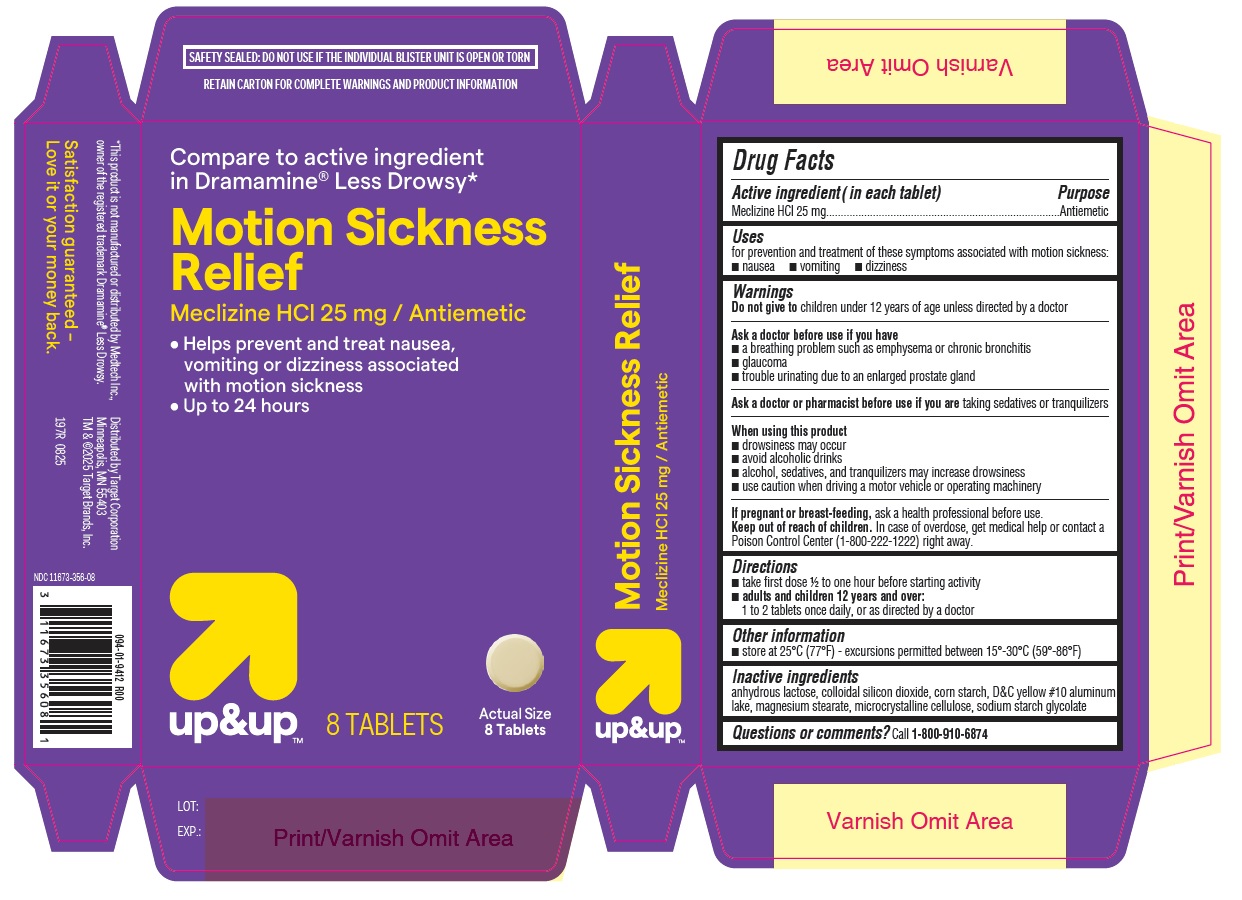 DRUG LABEL: Motion Sickness Relief
NDC: 11673-356 | Form: TABLET
Manufacturer: TARGET CORPORATION
Category: otc | Type: HUMAN OTC DRUG LABEL
Date: 20250904

ACTIVE INGREDIENTS: MECLIZINE HYDROCHLORIDE 25 mg/1 1
INACTIVE INGREDIENTS: SILICON DIOXIDE; MAGNESIUM STEARATE; D&C YELLOW NO. 10 ALUMINUM LAKE; MICROCRYSTALLINE CELLULOSE; ANHYDROUS LACTOSE; STARCH, CORN; SODIUM STARCH GLYCOLATE TYPE A

Target-197R-Meclizine HCl Tablets

Drug Facts

Active ingredient (in each tablet)

Meclizine HCl 25 mg

Purpose

Antiemetic

Uses

for prevention and treatment of these symptoms associated with motion sickness:

- nausea
- vomiting
- dizziness

Warnings

DO NOT USE

Do not give to children under 12 years of age unless directed by a doctor

Ask a doctor before use if you have

- a breathing problem such as emphysema or chronic bronchitis
- glaucoma
- trouble urinating due to an enlarged prostate gland

Ask a doctor or pharmacist before use if you are taking sedatives or tranquilizers

When using this product

- drowsiness may occur
- avoid alcoholic drinks
- alcohol, sedatives, and tranquilizers may increase drowsiness
- use caution when driving a motor vehicle or operating machinery

PREGNANCY OR BREAST FEEDING

If pregnant or breast-feeding, ask a health professional before use.

Keep out of reach of children.

In case of overdose, get medical help or contact a Poison Control Center (1-800-222-1222) right away.

Directions

- take first dose ½ to one hour before starting activity
- adults and children 12 years and over: 1 to 2 tablets once daily, or as directed by a doctor

Other information

- store at 25℃ (77℉) – excursions permitted between 15°-30℃ (59°-86℉)

INACTIVE INGREDIENT

Inactive ingredients anhydrous lactose, colloidal silicon dioxide, corn starch, D&C yellow #10 aluminum lake, magnesium stearate, microcrystalline cellulose, sodium starch glycolate

Questions or comments? Call 1-800-910-6874

PACKAGE LABEL

Motion Sickness Relief Tablets 8ct